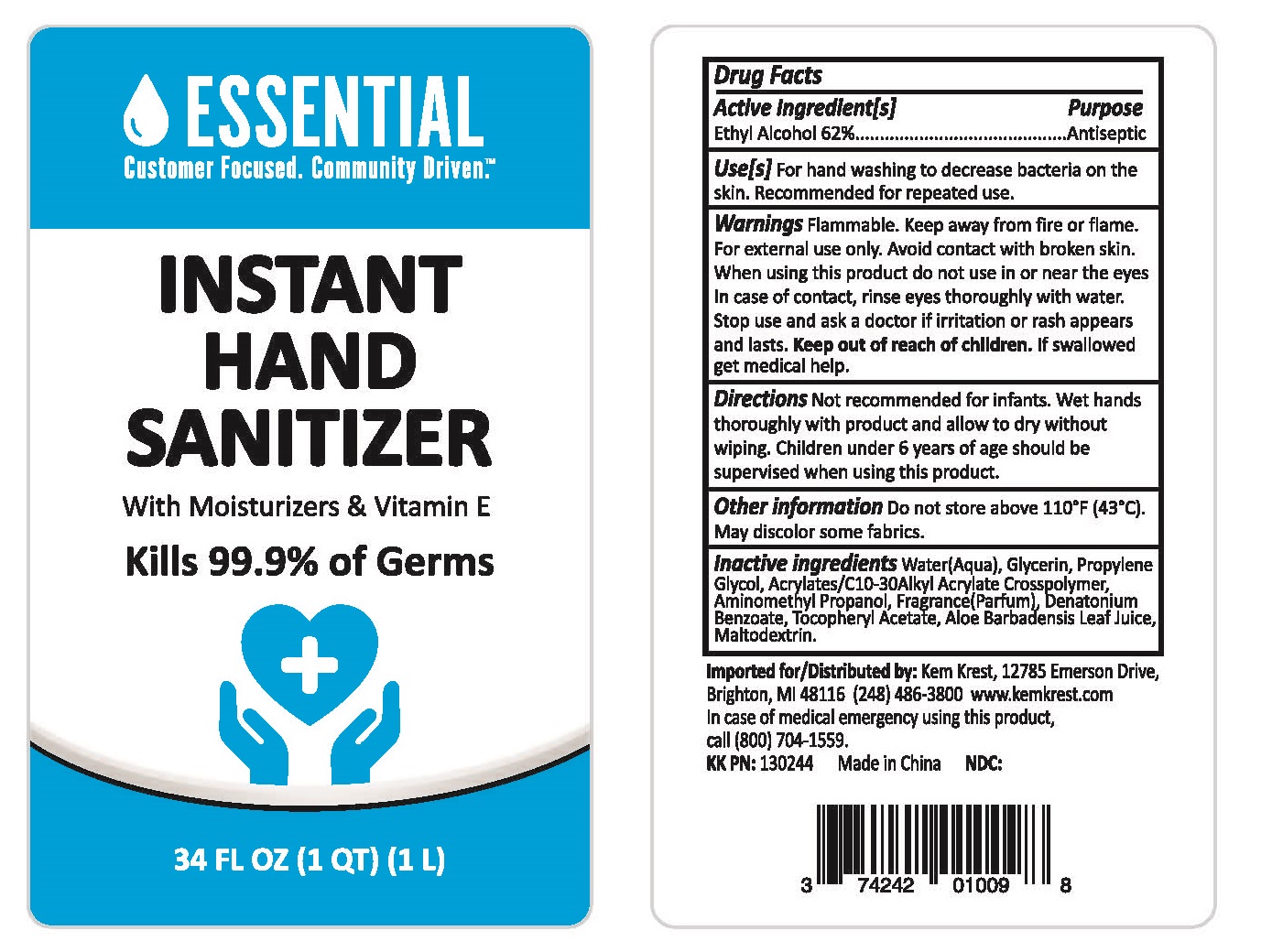 DRUG LABEL: Hand Sanitizer
NDC: 74242-134 | Form: GEL
Manufacturer: Kem Krest LLC
Category: otc | Type: HUMAN OTC DRUG LABEL
Date: 20200720

ACTIVE INGREDIENTS: ALCOHOL 62 mL/100 mL
INACTIVE INGREDIENTS: MALTODEXTRIN; ALOE VERA LEAF; WATER; GLYCERIN; PROPYLENE GLYCOL; CARBOMER COPOLYMER TYPE A (ALLYL PENTAERYTHRITOL CROSSLINKED); AMINOMETHYLPROPANOL; DENATONIUM BENZOATE; .ALPHA.-TOCOPHEROL ACETATE

Active Ingredient[s]

Ethyl Alcohol 62%

Purpose

Antiseptic

Use[s]

For hand washing to decrease bacteria on the skin. Recommended for repeated use.

Warnings

Flammable. Keep away from fire or flame. For external use only. Avoid contact with broken skin.

When using this product do not use in or near the eyes. In case of contact, rinse eyes thoroughly with water.

Stop use and ask a doctor if irritation or rash appears and lasts.

Keep out of reach of children.

If swallowed get medical help.

Directions

Not recommended for infants. Wet hands thoroughly with product and allow to dry without wiping. Children under 6 years of age should be supervised when using this product.

Other information

Do not store above 110 F (43°C). May discolor some fabrics.

Inactive ingredients

Water(Aqua), Glycerin, propylene Glycol, Acrylates/C10-30Alkyl Acrylate Crosspolymer, Aminomethyl Propanol, fragrance(Parfum), Denatonium Benzoate, Tocopheryl Acetate, Aloe Barbadensis Leaf Juice, Maltodextrin.